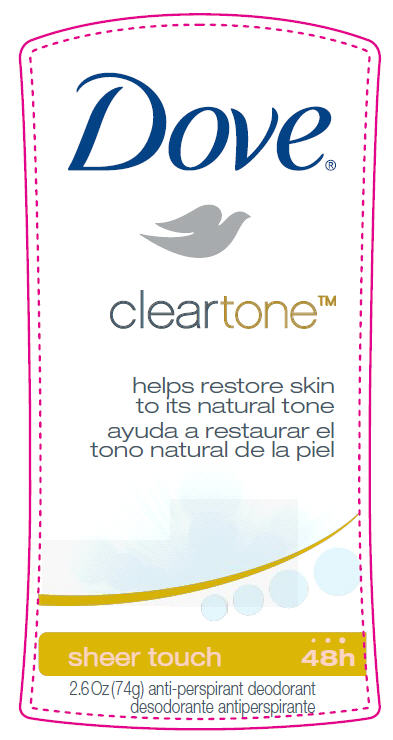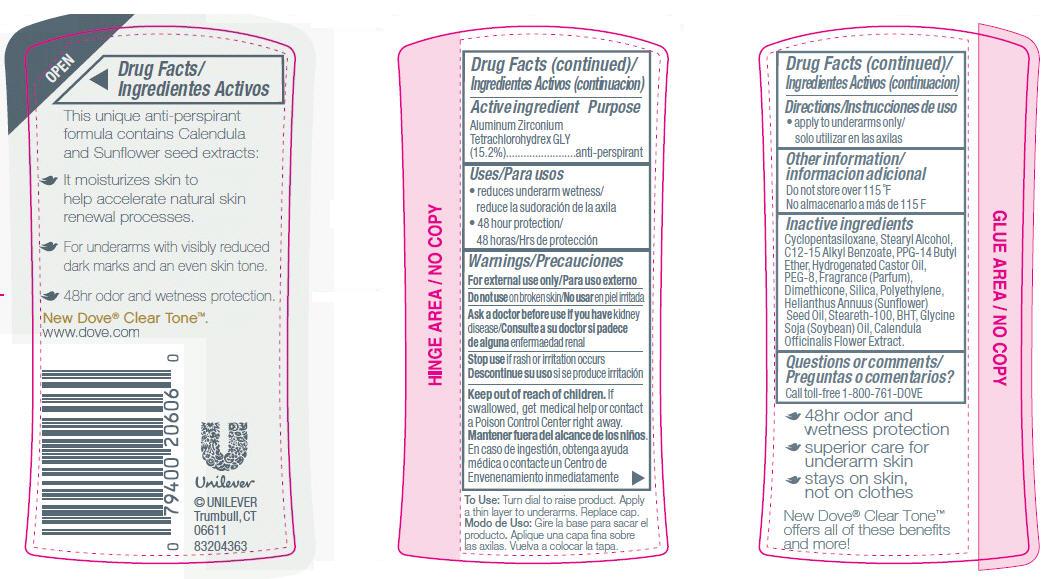 DRUG LABEL: Dove
NDC: 64942-1223 | Form: STICK
Manufacturer: Conopco Inc. d/b/a Unilever
Category: otc | Type: HUMAN OTC DRUG LABEL
Date: 20181212

ACTIVE INGREDIENTS: ALUMINUM ZIRCONIUM TETRACHLOROHYDREX GLY 15.2 g/100 g
INACTIVE INGREDIENTS: CYCLOMETHICONE 5; PPG-14 BUTYL ETHER; STEARYL ALCOHOL; HYDROGENATED CASTOR OIL; DIMETHICONE; BUTYLATED HYDROXYTOLUENE; STEARETH-100; SUNFLOWER OIL; SILICON DIOXIDE; POLYETHYLENE GLYCOL 400; ALKYL (C12-15) BENZOATE; SOYBEAN OIL; CALENDULA OFFICINALIS FLOWER

Dove Cleartone Sheer Touch Antiperspirant Deodorant

Active Ingredient

Aluminum Zirconium Tetrachlorohydrex GLY (15.2%)

Purpose

anti-perspirant

Uses/Para usos

· reduces underarm wetness/ reduce la sudoración de la axila

· 48 hour protection/48 horas/Hrs de protección

Warnings/Precauciones
For External Use Only/Para uso externo

Ask a doctor before use if you have kidney disease/

Consulte a su doctor si padece de alguna enfermaedad renal

Do not use on broken skin/

No usar en piel irritada

Stop use if rash or irritation occurs

Descontinue su uso si se produce irritación

Keep out of reach of children. If swallowed, get medical help or contact a Poison Control Center right away.

Mantener fuera del alcance de los niños. En caso de ingestión, obtenga ayuda médica o contacte un Centro de Envenenamiento inmediatamente.

Inactive ingredients

Ingredients: Cyclopentasiloxane, Stearyl Alcohol, C12-15 Alkyl Benzoate, PPG-14 Butyl Ether, Hydrogenated Castor Oil, PEG-8, Fragrance (Parfum), Dimethicone, Silica, Polyethylene, Helianthus Annuus (Sunflower) Seed Oil, Steareth-100,
BHT, Glycine Soja (Soybean) Oil, Calendula Officinalis Flower Extract.

Directions/Instrucciones de uso

· apply to underarms only/ solo utilizar en las axilas

Questions or comments/ Preguntas o comentarios?

Call toll-free 1-800-761-DOVE